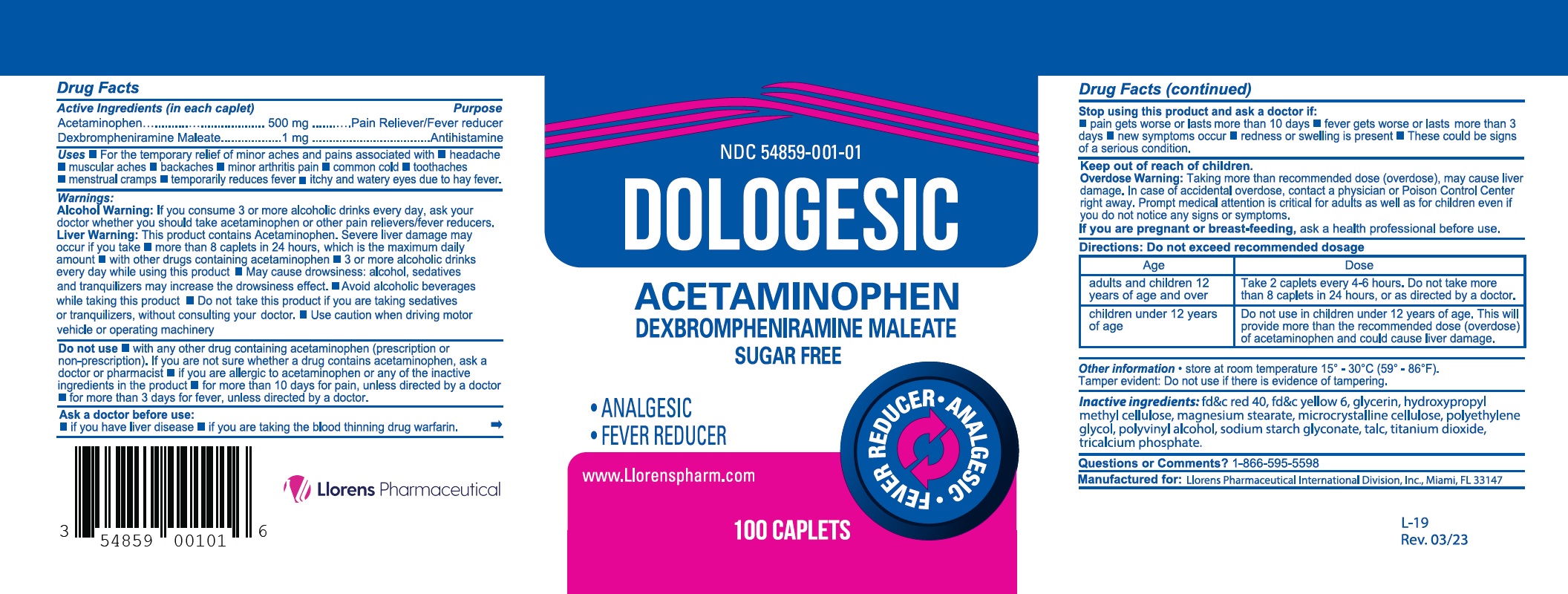 DRUG LABEL: Dologesic
NDC: 54859-001 | Form: TABLET
Manufacturer: Llorens Pharmaceutical International Division
Category: otc | Type: HUMAN OTC DRUG LABEL
Date: 20251231

ACTIVE INGREDIENTS: ACETAMINOPHEN 500 mg/1 1; DEXBROMPHENIRAMINE MALEATE 1 mg/1 1
INACTIVE INGREDIENTS: FD&C RED NO. 40; FD&C YELLOW NO. 6; HYDROXYPROPYL METHYLCELLULOSE; MAGNESIUM STEARATE; CELLULOSE, MICROCRYSTALLINE; POLYETHYLENE GLYCOL, UNSPECIFIED; SODIUM STARCH GLYCOLATE TYPE A CORN; TITANIUM DIOXIDE; TALC; TRICALCIUM PHOSPHATE; POLYVINYL ALCOHOL; GLYCERIN

Llorens-Dologesic 001

Active Ingredients

(in each caplet)

Acetaminophen 500 mg

Dexbrompheniramine Maleate 1 mg

Purpose

Pain reliever/fever reducer

antihistamine

Uses

- For the temporary relief of minor aches and pains associated with
- headache
- muscular aches
- backaches
- minor arthritis pain
- common cold
- toothaches
- menstrual cramps
- temporarily reduces fever
- itchy and watery eyes due to hay fever

Warnings

Alcohol Warning: If you consumer 3 or more alcoholic drinks every day, ask your doctor whether you should take acetaminophen or other pain relievers/fever reducers.

Liver Warning: This product contains acetaminophen. Sever liver damage may occur if you take

- more than 8 capsules in 24 hours, which is the maximum daily amount
- with other drugs containing acetaminphen
- 3 or more alcoholic drinks every day while using this product
- May cause drowsiness:: alcohol, sedatives and tranquilizers may increase the drowsiness effect.
- Avoid alcoholic beverages while taking this product
- Do not take this product if you are taking sedatives or tranquilizers, without consulting your doctor.
- Use caution when driving motor vehicle or operating machinery

Do not use

- with any other drug containing acetaminphen (prescription or non-prescription). If you are not sure whether a drug contains acetaminphen ask a doctor or pharmacist
- if you are allergic to acetaminophen or any of the inactive ingredients in the product
- for more than 10 days for pain, unless directed by a doctor
- for more than 3 days for fever, unless directed by a doctor

Ask a doctor before use:

- if you have liver disease
- if you are taking the blood thinning drug warafin

Stop using this product and ask a doctor if:

- pain gets worse or last more than 10 days
- fever gets worse or last more than 3 days
- new symptoms occur
- redness or swelling is present
- these could be signs of a serious condition

Keep out of reach of children

PREGNANCY OR BREAST FEEDING

If you are pregnant or breast-feeding, ask a health professional before use.

Directions

Overdose Warning: Taking more than recommended dose (overdose), may cause liver damage. In case of accidental overdose, contact a physician or Poison Control Center right away. Prompt medical attention is critical for adults as well as for children even if you do not notice any signs or symptoms

Do not exceed recommended dosage

Age | Dose
adults and children 12 years of age and over | Take 2 caplets every 4-6 hours. Do not take more than 8 caplets in 24 hours, or as directed by a doctor
children under 12 years of age | Do not use in children under 12 years of age. This will provide more than the recommended dose (overdose) of acetaminphen and could cause liver damage

Inactive ingredients

FD&C Red #40, FD&C Yellow #6, glycerin, hydrocypropyl methyl cellulose, magnesium stearate, microcrystaline cellulose,polyethylene glycol, polyvinyl alcohol, sodium starch glycolate, talc, titanium dioxide, tricalcium phosphate

Questions or comments

1-866-595-5598

RECENT MAJOR CHANGES

Added "itchy and watery eyes due to hay fever" in Uses section